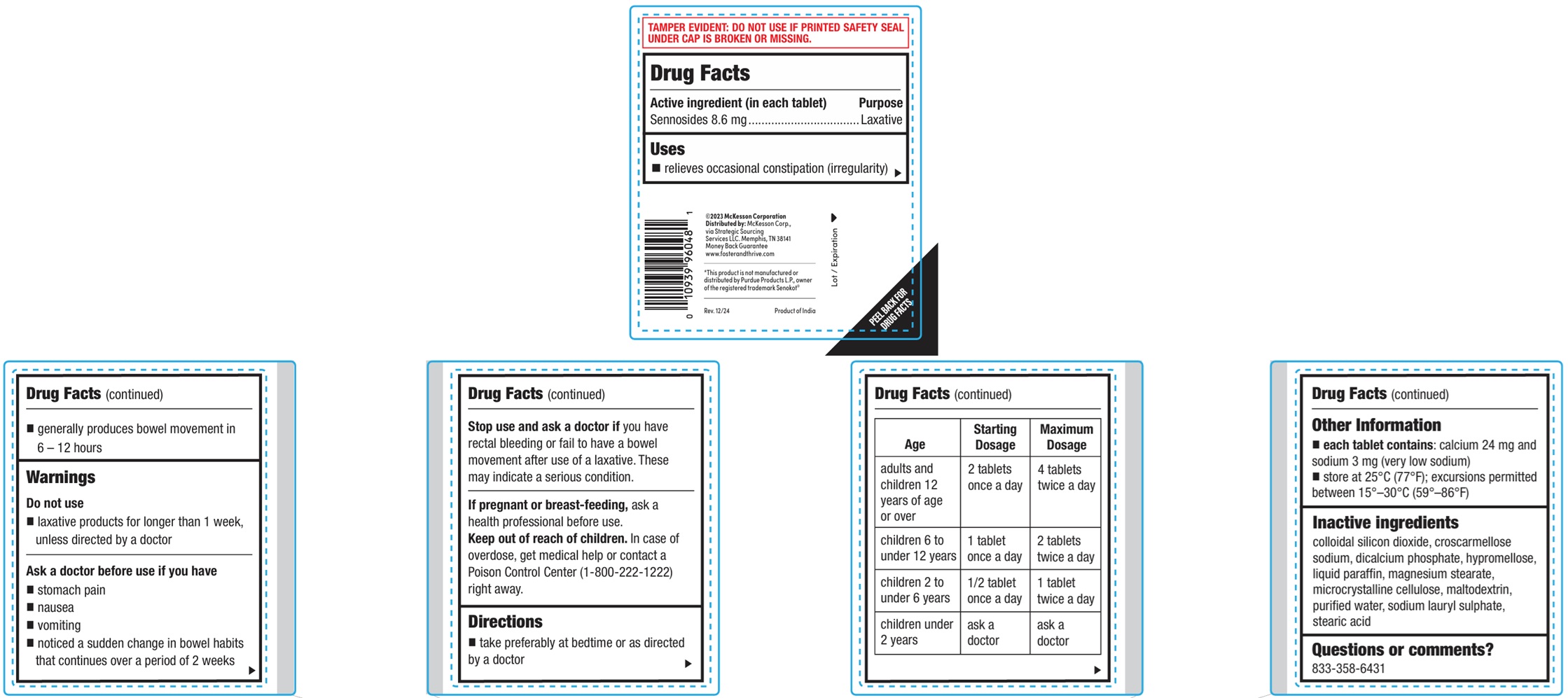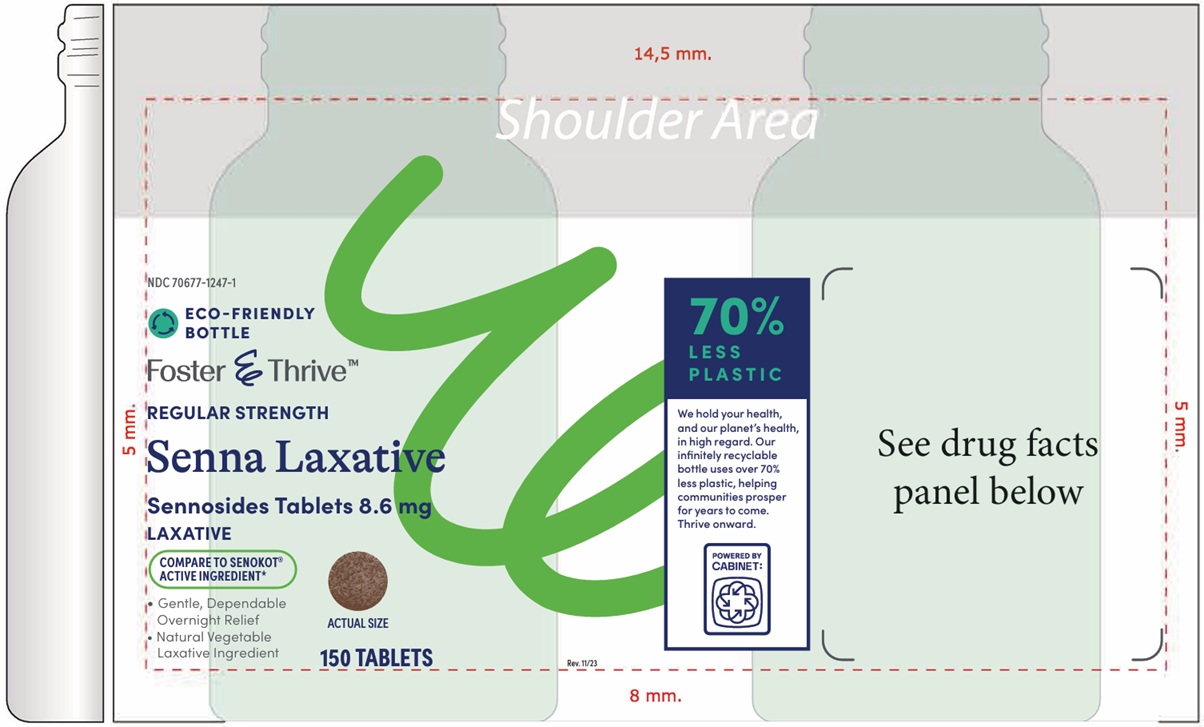 DRUG LABEL: Senna Laxative
NDC: 70677-1247 | Form: TABLET
Manufacturer: Strategic Sourcing Services LLC
Category: otc | Type: HUMAN OTC DRUG LABEL
Date: 20260129

ACTIVE INGREDIENTS: SENNOSIDES 8.6 mg/1 1
INACTIVE INGREDIENTS: SILICON DIOXIDE; CROSCARMELLOSE SODIUM; CALCIUM PHOSPHATE, DIBASIC, ANHYDROUS; PARAFFIN; MAGNESIUM STEARATE; CELLULOSE, MICROCRYSTALLINE; MALTODEXTRIN; WATER; SODIUM LAURYL SULFATE; STEARIC ACID

Senna Laxative

Other information

• each tablet contains:calcium 24mg and sodium 3mg (Very Low Sodium)

• store at 25°C (77°F); excursions permitted between 15°-30°C (59°-86°F)